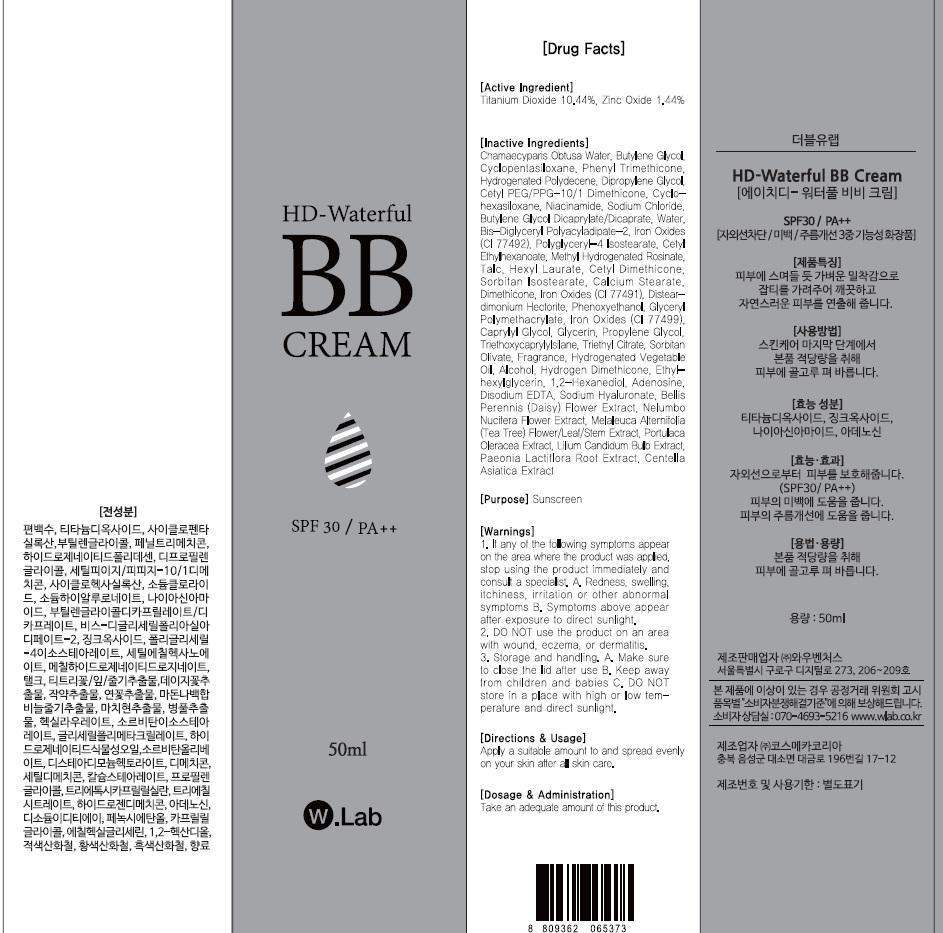 DRUG LABEL: HD WATERFUL BB
NDC: 69894-290 | Form: CREAM
Manufacturer: WOW VENTURES
Category: otc | Type: HUMAN OTC DRUG LABEL
Date: 20150626

ACTIVE INGREDIENTS: Titanium Dioxide 5.22 mg/50 mL; Zinc Oxide 0.72 mg/50 mL
INACTIVE INGREDIENTS: Butylene Glycol; Phenyl Trimethicone

ACTIVE INGREDIENT

Active Ingredient: Titanium Dioxide 10.44%, Zinc Oxide 1.44%

INACTIVE INGREDIENT

Inactive Ingredients: Chamaecyparis Obtusa Water, Butylene Glycol, Cyclopentasiloxane, Phenyl Trimethicone, Hydrogenated Polydecene, Dipropylene Glycol, Cetyl PEG/PPG-10/1 Dimethicone, Cyclohexasiloxane, Niacinamide, Sodium Chloride, Butylene Glycol Dicaprylate/Dicaprate, Water, Bis-Diglyceryl Polyacyladipate-2, Iron Oxides (CI 77492), Polyglyceryl-4 Isostearate, Cetyl Ethylhexanoate, Methyl Hydrogenated Rosinate, Talc, Hexyl Laurate, Cetyl Dimethicone, Sorbitan Isostearate, Calcium Stearate, Dimethicone, Iron Oxides (CI 77491), Disteardimonium Hectorite, Phenoxyethanol, Glyceryl Polymethacrylate, Iron Oxides (CI 77499), Caprylyl Glycol, Glycerin, Propylene Glycol, Triethoxycaprylylsilane, Triethyl Citrate, Sorbitan Olivate, Fragrance, Hydrogenated Vegetable Oil, Alcohol, Hydrogen Dimethicone, Ethylhexylglycerin, 1,2-Hexanediol, Adenosine, Disodium EDTA, Sodium Hyaluronate, Bellis Perennis (Daisy) Flower Extract, Nelumbo Nucifera Flower Extract, Melaleuca Alternifolia (Tea Tree) Flower/Leaf/Stem Extract, Portulaca Oleracea Extract, Lilium Candidum Bulb Extract, Paeonia Lactiflora Root Extract, Centella Asiatica Extract

PURPOSE

Purpose: Sunscreen

WARNINGS

Warnings: 1. If any of the following symptoms appear on the area where the product was applied, stop using the product immediately and consult a specialist. A. Redness, swelling, itchiness, irritation or other abnormal symptoms B. Symptoms above appear after exposure to direct sunlight 2. DO NOT use the product on an area with wound, eczema, or dermatitis 3. Storage and handling. A. Make sure to close the lid after use B. Keep away from children and babies C. DO NOT store in a place with high or low temperature and direct sunlight

DESCRIPTION

Directions & Usage: Apply a suitable amount to and spread evenly on your skin after all skin care.

Dosage & Administration: Take an adequate amount of this product.